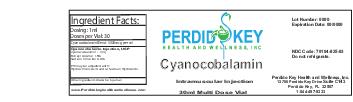 DRUG LABEL: Cyanocobalamin
NDC: 70104-825 | Form: INJECTION
Manufacturer: Perdido Key Health and Wellness Inc
Category: prescription | Type: HUMAN PRESCRIPTION DRUG LABEL
Date: 20151120

ACTIVE INGREDIENTS: 8-EPI-CYANOCOBALAMIN 1 mg/1 mL

DOSAGE FORMS AND STRENGTHS

1ml